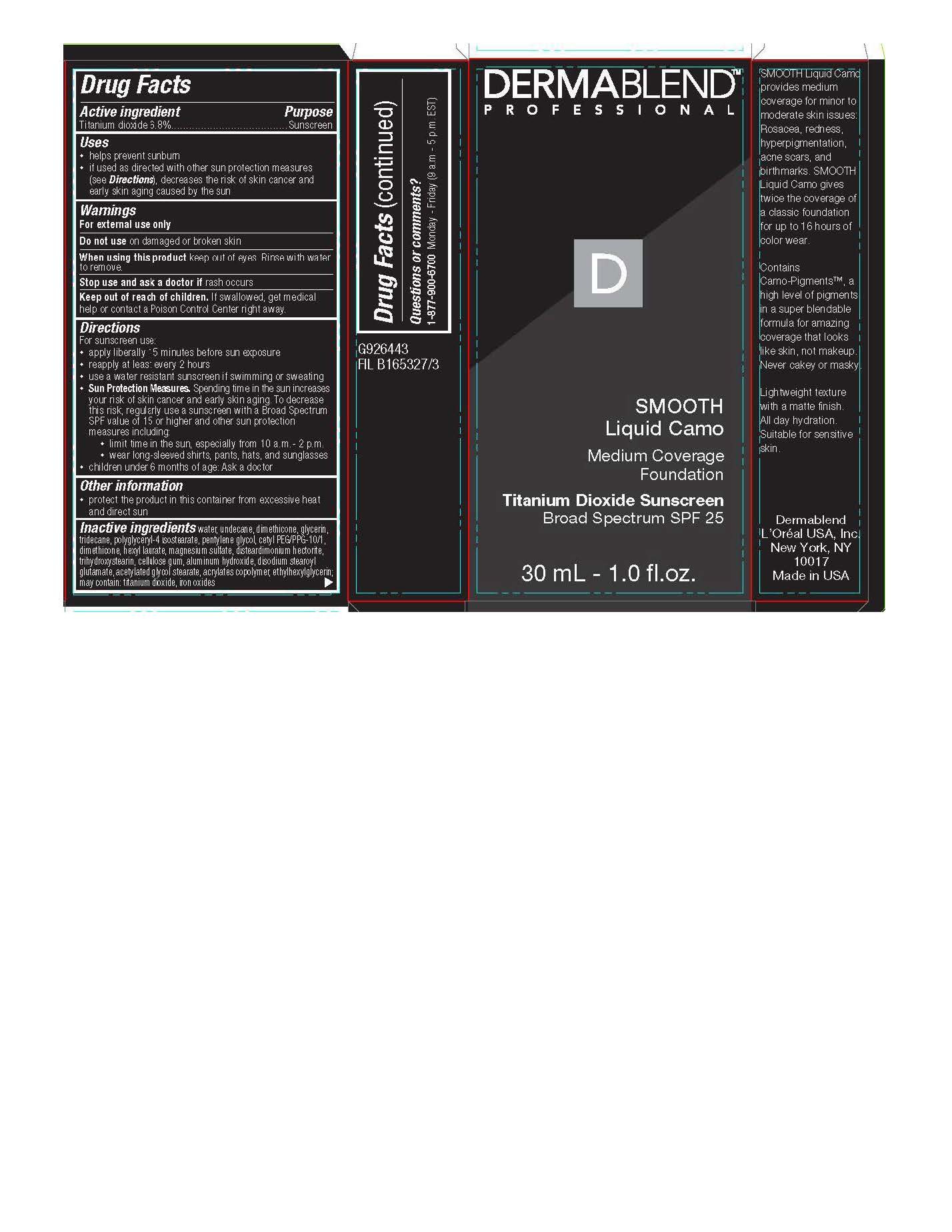 DRUG LABEL: Sunscreen
NDC: 84203-001 | Form: LIQUID
Manufacturer: Baxter of California, LLC
Category: otc | Type: HUMAN OTC DRUG LABEL
Date: 20250724

ACTIVE INGREDIENTS: TITANIUM DIOXIDE 0.068 g/1 mL
INACTIVE INGREDIENTS: FERRIC OXIDE RED; ETHYLHEXYLGLYCERIN; WATER; UNDECANE; DIMETHICONE; GLYCERIN; TRIDECANE; POLYGLYCERYL-4 ISOSTEARATE; PENTYLENE GLYCOL; CETYL PEG/PPG-10/1 DIMETHICONE (HLB 2); HEXYL LAURATE; MAGNESIUM SULFATE, UNSPECIFIED FORM; DISTEARDIMONIUM HECTORITE; TRIHYDROXYSTEARIN; CARBOXYMETHYLCELLULOSE SODIUM, UNSPECIFIED FORM; ALUMINUM HYDROXIDE; DISODIUM STEAROYL GLUTAMATE; ACETYLATED GLYCOL STEARATE

Smooth Liquid Camo Titanium Dioxide Sunscreen SPF 25

Active Ingredients

Octisalate 3.2%

Octocrylene 6%

Purpose

Sunscreen

Uses

Helps prevent sunburn

if used as directed with other sun protection measures (see directions), decreases the risk of skin cancer and early skin aging caused by the sun

Warnings

For external use only

Do not use

on damamged skin or broken skin

When using this product

Keep out of eyes.

Rinse with water to remove

Stop use and ask doctor if

rash occurs

Keep out of reach of children

If swallowed, get medical help or contact a Poison Control Center right away.

Directions

For sunscreen use:

- apply liberally 15 minutes before sun exposure
- reapply at least every 2 hours
- use a water resistant sunscreen if swimming or sweating
- Sun Protection Measures. Spending time in the sun increases your risk of skin cancer and early skin aging. To decrease this risk, regularly use a sunscreen with a Broad Spectrum SPF value of 15 or higher and other sun protection measures including
  - limit time in the sun, especially from 10am-2pm
  - wear long sleeved shirts, pants, hats, and sunglasses
  - children under 6 months of age: Ask a doctor

Other information

protect the product in this container from excessive heat and direct sun

Inactive ingredients

water, undecane, dimethicone, glycerin, tridecane, polyglyceryl-4 isostearate, pentylene
glycol, cetyl PEG/PPG-10/1, hexyl laurate, magnesium sulfate, disteardimonium hectorite,
trihydroxystearin, cellulose gum, aluminum hydroxide, disodium stearoyl glutamate,
acetylated glycol stearate, acrylates copolymer, ethylhexylglyceerin; may contain:
titanium dioxide, iron oxides

Questions or Comments?

1-877-900-6700
Monday - Friday (9 a.m. - 5 p.m. EST)